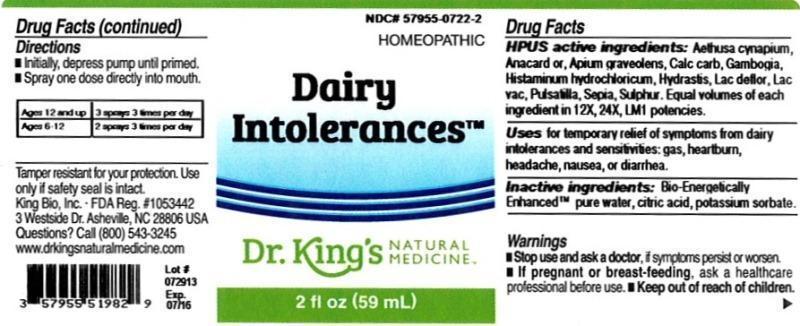 DRUG LABEL: Dairy Intolerances
NDC: 57955-0722 | Form: LIQUID
Manufacturer: King Bio Inc.
Category: homeopathic | Type: HUMAN OTC DRUG LABEL
Date: 20131125

ACTIVE INGREDIENTS: AETHUSA CYNAPIUM 12 [hp_X]/59 mL; SEMECARPUS ANACARDIUM JUICE 12 [hp_X]/59 mL; CELERY SEED 12 [hp_X]/59 mL; OYSTER SHELL CALCIUM CARBONATE, CRUDE 12 [hp_X]/59 mL; GAMBOGE 12 [hp_X]/59 mL; HISTAMINE DIHYDROCHLORIDE 12 [hp_X]/59 mL; GOLDENSEAL 12 [hp_X]/59 mL; SKIM MILK 12 [hp_X]/59 mL; COW MILK 12 [hp_X]/59 mL; PULSATILLA VULGARIS 12 [hp_X]/59 mL; SEPIA OFFICINALIS JUICE 12 [hp_X]/59 mL; SULFUR 12 [hp_X]/59 mL
INACTIVE INGREDIENTS: WATER; CITRIC ACID MONOHYDRATE; POTASSIUM SORBATE

Dairy Intolerances™

ACTIVE INGREDIENT

Drug Facts__________________________________________________________________________________________________________

HPUS active ingredients: Aethusa cynapium, Anacardium orientale, Apium graveolens, Calcarea carbonica, Gambogia, Histaminum hydrochloricum, Hydrastis canadensis, Lac defloratum, Lac vaccinum, Pulsatilla, Sepia, Sulphur. Equal volumes of each ingredient in 12X, 24X, LM1 potencies.

INDICATIONS AND USAGE

Uses for temporary relief of symptoms from dairy intolerances and sensitivities: gas, heartburn, headache, nausea, or diarrhea.

Inactive Ingredients:

Bio-Energetically Enhanced™ pure water, citric acid and potassium sorbate.

Warnings

- Stop use and ask your doctor if symptoms persist or worsen.

- If pregnant or breast-feeding, ask a healthcare professional before use.

- Keep out of reach of children

Directions

- Initially, depress pump until primed.
- Spray one dose directly into mouth.
- Ages 12 and up- 3 sprays 3 times per day.
- Ages 6-12- 2 sprays 3 times per day.

OTHER SAFETY INFORMATION

Tamper resistant for your protection. Use only if safety seal is intact.

PURPOSE

Uses for temporary relief of symptoms from dairy intolerances and sensitivities:

- gas
- heartburn
- headache
- nausea
- diarrhea